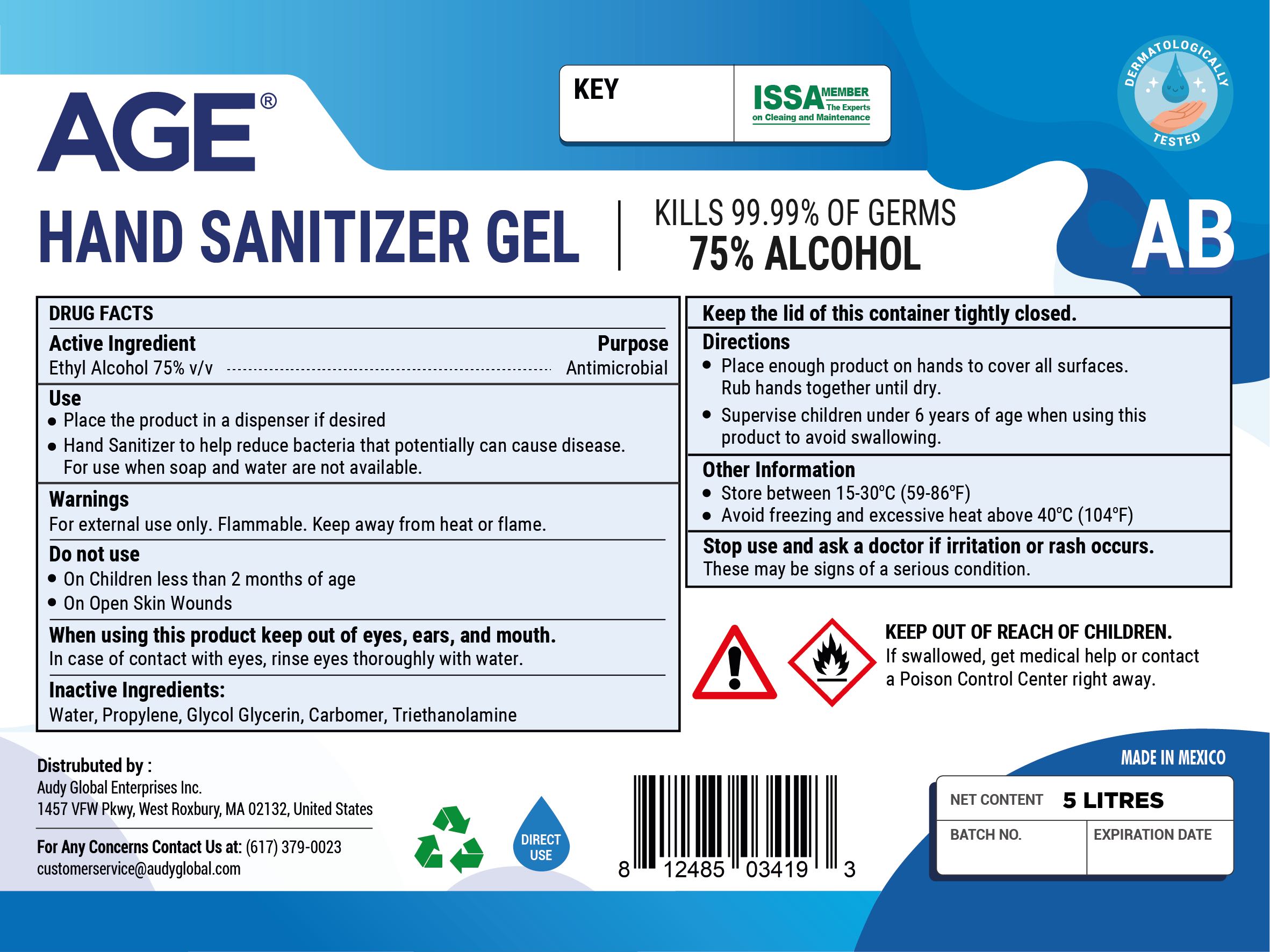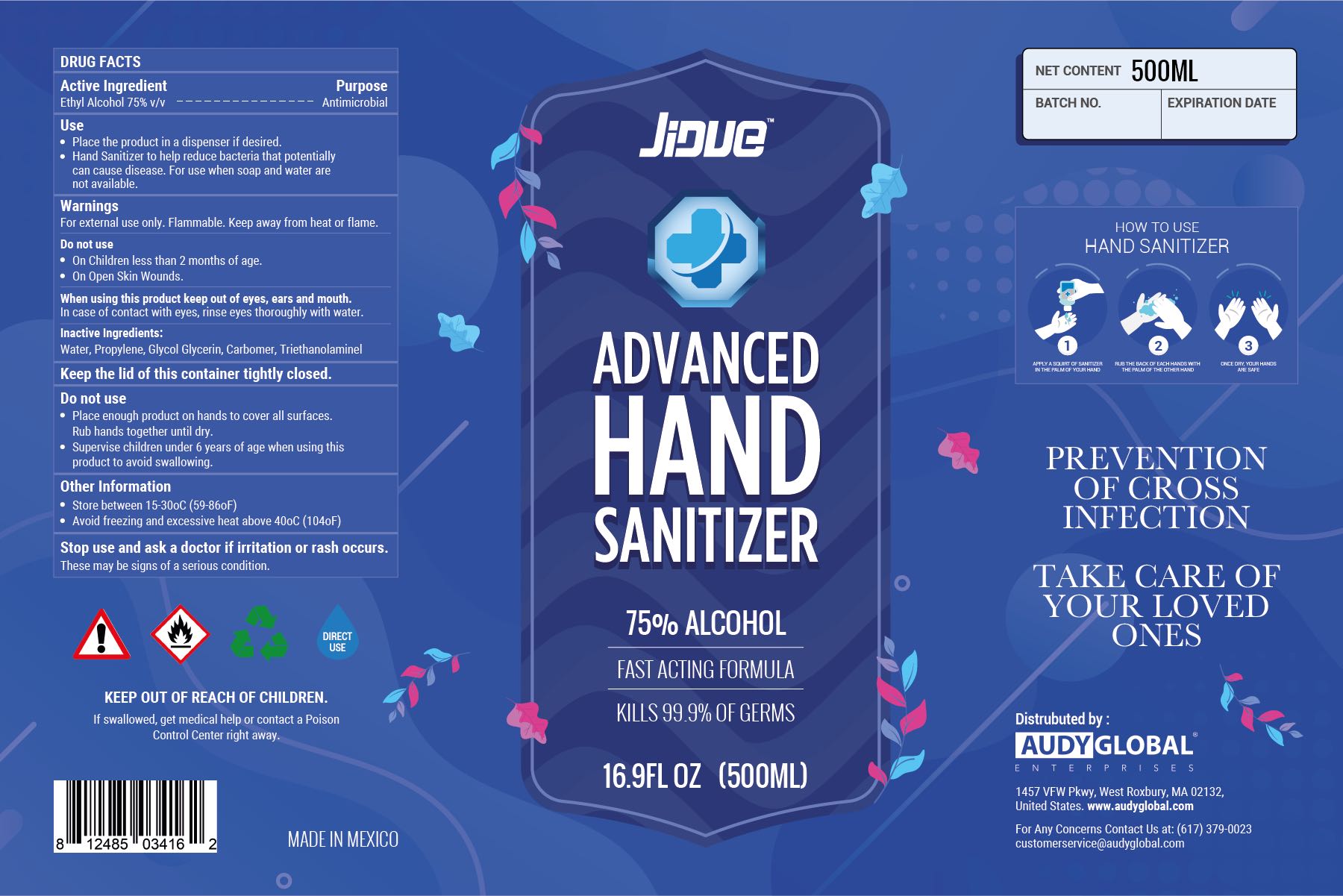 DRUG LABEL: Hand Sanitizer
NDC: 75778-003 | Form: GEL
Manufacturer: Audy Global Enterprises Inc.
Category: otc | Type: HUMAN OTC DRUG LABEL
Date: 20200501

ACTIVE INGREDIENTS: ALCOHOL 75 mL/100 mL
INACTIVE INGREDIENTS: POLYACRYLIC ACID (800000 MW) 0.5 mL/100 mL; PROPYLENE GLYCOL 3 mL/100 mL; TROLAMINE 0.3 mL/100 mL; WATER 20.2 mL/100 mL; GLYCERIN 1 mL/100 mL

Active Ingredient(s)

Ethyl Alcohol 75% v/v.

Purpose: Antimicrobial

Use

Place product in a dispenser if desired

Hand Sanitizer to help reduce bacteria that potentially can cause disease. For use when soap and water are not available.

Warnings

For external use only. Flammable. Keep away from heat or flame

Do not use

- on Children less than 2 months of age
- on open skin wounds

When using this product keep out of eyes, ears, and mouth. In case of contact with eyes, rinse eyes thoroughly with water.

Stop use and ask a doctor if irritation or rash occurs. These may be signs of a serious condition.

Keep out of reach of children. If swallowed, get medical help or contact a Poison Control Center right away.

Directions

- Place enough product on hands to cover all surfaces. Rub hands together until dry.
- Supervise children under 6 years of age when using this product to avoid swallowing.

Other information

- Store between 15-30C (59-86F)
- Avoid freezing and excessive heat above 40C (104F)

Inactive ingredients

Water (Aqua) , Glycerin, Carbomer, Phenoxyethanol, Aminomethyl propanol

Package Label - Principal Display Panel

500 ml NDC: 75778-003-50

5 L NDC: 75778-003-55